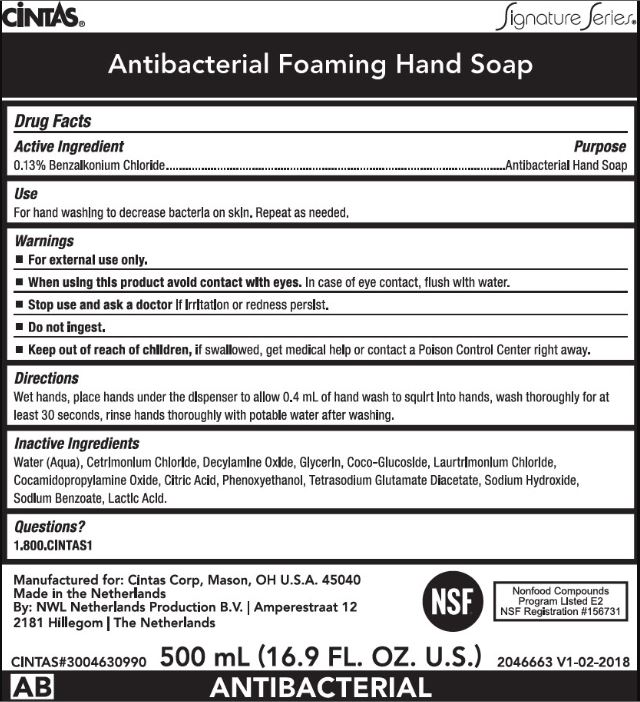 DRUG LABEL: Foam Antibacterial Hand Wash
NDC: 42961-953 | Form: SOAP
Manufacturer: Cintas Corporation
Category: otc | Type: HUMAN OTC DRUG LABEL
Date: 20221229

ACTIVE INGREDIENTS: Benzalkonium Chloride 13 mg/10 mL
INACTIVE INGREDIENTS: Water; Cetrimonium Chloride; Decylamine Oxide; Glycerin; Coco Glucoside; Laurtrimonium Chloride; Cocamidopropylamine Oxide; Citric Acid Monohydrate; Phenoxyethanol; Tetrasodium Glutamate Diacetate; Sodium Hydroxide; Sodium Benzoate; Lactic Acid, Unspecified Form

Foam Antibacterial Hand Wash

Drug Facts

Active Ingredient

0.13% Benzalkonium Chloride

Purpose

Antibacterial Hand Soap

Use

For hand washing to decrease bacteria on skin. Repeat as needed.

Warnings

- For external use only.

- When using this product avoid contact with eyes. In case of eye contact, flush with water.

- Stop use and ask a doctor if irritation or redness persist.

- Do not ingest.

- Keep out of reach of children, if swallowed, get medical help or contact a Poison Control Center right away.

Directions

Wet hands, place hands under the dispenser to allow 0.4 ml of hand wash to squirt into hands, wash thoroughly for at least 30 seconds, rinse hands thoroughly with potable water after washing.

Inactive Ingredients

Water (Aqua), Cetrimonium Chloride, Oecylamine Oxide, Glycerin, Coco-Glucoside, Laurtrimonium Chloride, Cocamidopropylamine Oxide, Citric Acid, Phenoxyethanol, Tetrasodium Glutamate Diacetate, Sodium Hydroxide, Sodium Benzoate, Lactic Acid.

Questions?

1.800.CINTAS1

PRINCIPAL DISPLAY PANEL - 500 mL Bag Label

CiNTAS®
Signature Series®

Antibacterial Foaming Hand Soap

CINTAS#3004630990
500 mL (16.9 FL. OZ. U.S.)
2046663 V1-02-2018

ANTIBACTERIAL